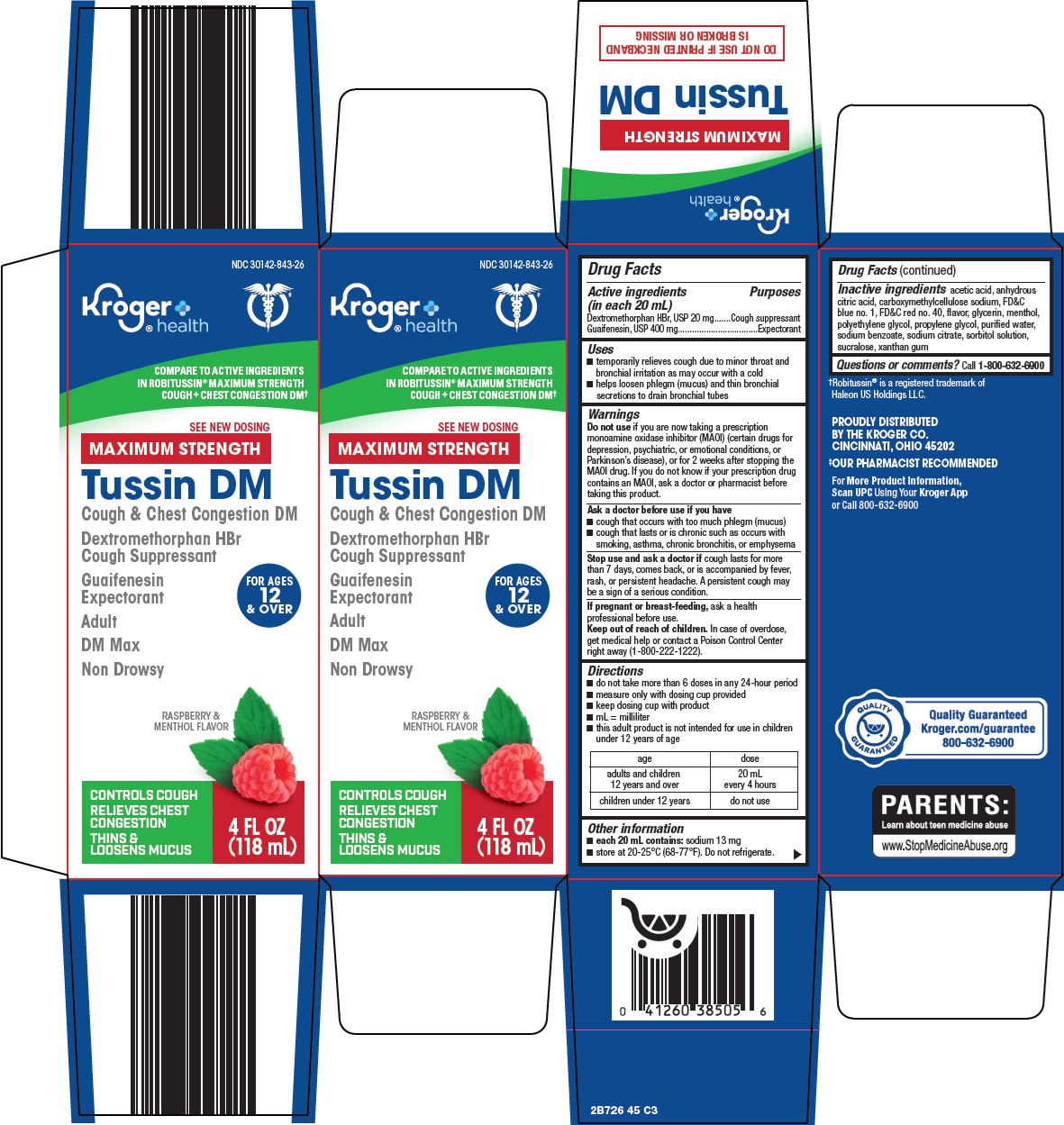 DRUG LABEL: tussin dm max
NDC: 30142-843 | Form: SOLUTION
Manufacturer: Kroger Company
Category: otc | Type: HUMAN OTC DRUG LABEL
Date: 20260219

ACTIVE INGREDIENTS: DEXTROMETHORPHAN HYDROBROMIDE 20 mg/20 mL; GUAIFENESIN 400 mg/20 mL
INACTIVE INGREDIENTS: ANHYDROUS CITRIC ACID; CARBOXYMETHYLCELLULOSE SODIUM, UNSPECIFIED; FD&C BLUE NO. 1; FD&C RED NO. 40; GLYCERIN; MENTHOL, UNSPECIFIED FORM; POLYETHYLENE GLYCOL, UNSPECIFIED; PROPYLENE GLYCOL; WATER; SODIUM BENZOATE; SODIUM CITRATE, UNSPECIFIED FORM; SORBITOL SOLUTION; SUCRALOSE; XANTHAN GUM

Kroger Co. Tussin DM Max Drug Facts

Active ingredients (in each 20 mL)

Dextromethorphan HBr, USP 20 mg

Guaifenesin, USP 400 mg

Purposes

Cough suppressant

Expectorant

Uses

- temporarily relieves cough due to minor throat and bronchial irritation as may occur with a cold
- helps loosen phlegm (mucus) and thin bronchial secretions to drain bronchial tubes

Warnings

Do not use

if you are now taking a prescription monoamine oxidase inhibitor (MAOI) (certain drugs for depression, psychiatric, or emotional conditions, or Parkinson’s disease), or for 2 weeks after stopping the MAOI drug. If you do not know if your prescription drug contains an MAOI, ask a doctor or pharmacist before taking this product.

Ask a doctor before use if you have

- cough that occurs with too much phlegm (mucus)
- cough that lasts or is chronic such as occurs with smoking, asthma, chronic bronchitis, or emphysema

Stop use and ask a doctor if

cough lasts for more than 7 days, comes back, or is accompanied by fever, rash, or persistent headache. A persistent cough may be a sign of a serious condition.

If pregnant or breast-feeding,

ask a health professional before use.

Keep out of reach of children.

In case of overdose, get medical help or contact a Poison Control Center right away (1-800-222-1222).

Directions

- do not take more than 6 doses in any 24-hour period
- measure only with dosing cup provided
- keep dosing cup with product
- mL = milliliter
- this adult product is not intended for use in children under 12 years of age

age | dose
adults and children 12 years and over | 20 mL every 4 hours
children under 12 years | do not use

Other information

- each 20 mL contains: sodium 13 mg
- store at 20-25°C (68-77°F). Do not refrigerate.

Inactive ingredients

acetic acid, anhydrous citric acid, carboxymethylcellulose sodium, FD&C blue no. 1, FD&C red no. 40, flavor, glycerin, menthol, polyethylene glycol, propylene glycol, purified water, sodium benzoate, sodium citrate, sorbitol solution, sucralose, xanthan gum

Questions or comments?

Call 1-800-632-6900

Package/Label Principal Display Panel

Kroger® health

COMPARE TO ACTIVE INGREDIENTS IN ROBITUSSIN® MAXIMUM STRENGTH COUGH + CHEST CONGESTION DM

SEE NEW DOSING

MAXIMUM STRENGTH

Tussin DM

Cough & Chest Congestion DM

Dextromethorphan HBr

Cough Suppressant

Guaifenesin Expectorant

FOR AGES 12 & OVER

Adult

DM Max

Non Drowsy

RASPBERRY & MENTHOL FLAVOR

CONTROLS COUGH

RELIEVES CHEST CONGESTION

THINS & LOOSENS MUCUS

4 FL OZ (118 mL)